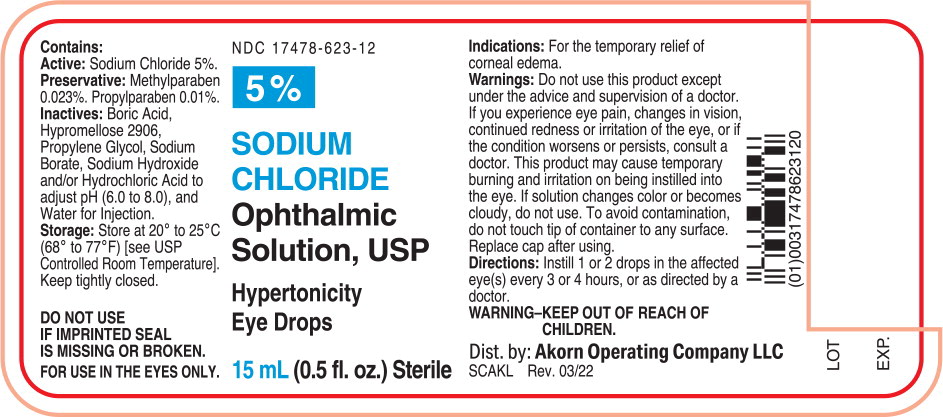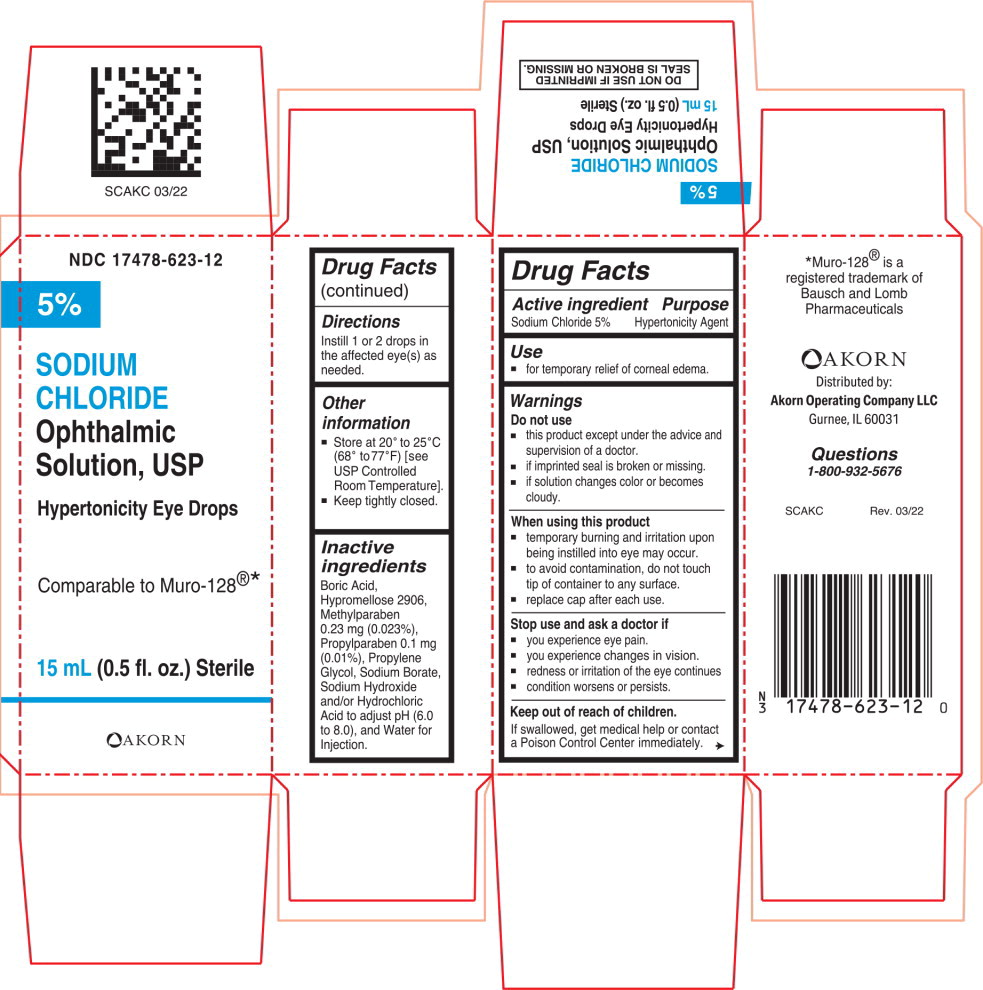 DRUG LABEL: Sodium Chloride
NDC: 17478-623 | Form: SOLUTION/ DROPS
Manufacturer: Akorn
Category: otc | Type: HUMAN OTC DRUG LABEL
Date: 20220701

ACTIVE INGREDIENTS: Sodium Chloride 50 mg/1 mL
INACTIVE INGREDIENTS: Boric Acid; Hypromelloses; Propylene Glycol; Sodium Borate; Sodium Hydroxide; Hydrochloric Acid; Water; Methylparaben; Propylparaben

Sodium Chloride Ophthalmic Solution, USP

Drug Facts

Active ingredient

Sodium Chloride 5%

Purpose

Hypertonicity Agent

Use

- for temporary relief of corneal edema.

Warnings

Do not use

- this product except under the advice and supervision of a doctor.
- if imprinted seal is broken or missing.
- if solution changes color or becomes cloudy.

When using this product

- temporary burning and irritation upon being instilled into eye may occur.
- to avoid contamination, do not touch tip of container to any surface
- replace cap after each use

Stop use and ask a doctor if

- you experience eye pain.
- you experience changes in vision.
- redness or irritation of the eye continues
- condition worsens or persists.

Keep out of reach of children.

If swallowed, get medical help or contact a Poison Control Center immediately.

Directions

Instill 1 or 2 drops in the affected eye(s) as needed.

Other information

- Store at 20° to 25°C (68° to77°F) [see USP Controlled Room Temperature].
- Keep tightly closed.

Inactive ingredients

Boric Acid, Hypromellose 2906, Methylparaben 0.23 mg (0.023%), Propylparaben 0.1 mg (0.01%), Propylene Glycol, Sodium Borate, Sodium Hydroxide and/or Hydrochloric Acid to adjust pH (6.0 to 8.0), and Water for Injection.

Principal Display Panel Text for Container Label:

NDC 17478-623-12
5%
SODIUM
CHLORIDE
Ophthalmic
Solution, USP

Hypertonicity
Eye Drops
15 mL (0.5 fl. oz.) Sterile

Principal Display Panel Text for Carton Label:

NDC 17478-623-12
5%
SODIUM
CHLORIDE
Ophthalmic
Solution, USP

Hypertonicity Eye Drops

Comparable to Muro-128®*
15 mL (0.5 fl. oz.) Sterile

Akorn Logo